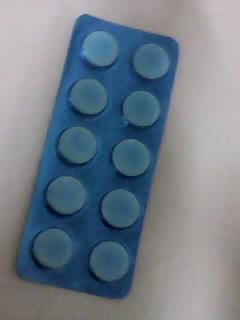 DRUG LABEL: APINOPHEN
NDC: 46084-061 | Form: TABLET
Manufacturer: A P J Laboratories Limited
Category: otc | Type: HUMAN OTC DRUG LABEL
Date: 20140102

ACTIVE INGREDIENTS: ACETAMINOPHEN 500 mg/1 1
INACTIVE INGREDIENTS: LACTOSE MONOHYDRATE 10 mg/1 1; STARCH, CORN 17 mg/1 1; GELATIN 2 mg/1 1; METHYLPARABEN 10 mg/1 1; PROPYLPARABEN 1 mg/1 1; MAGNESIUM STEARATE 10 mg/1 1; TALC 10 mg/1 1; SODIUM STARCH GLYCOLATE TYPE A POTATO 20 mg/1 1; SILICON DIOXIDE 1 mg/1 1

active ingredient

Acetaminophen 500 mg

purpose

Pain reliever/fever reducer

keep out of reach of children

Overdose warning:

In case of overdose, get medical help or contact a Poison Control Center right away (1-800-222-1222). Quick medical attention is critical for adults as well as for children even if you do not notice any signs or symptoms.

uses

temporarily relieves minor aches and pains due to:
the common cold
headache
backache
minor pain of arthritis
toothache
muscular aches
premenstrual and menstrual cramps
temporarily reduces fever

warning

Liver warning:

This product contains acetaminophen. The maximum daily dose of this product is 6 caplets (3,000 mg) in 24 hours. Severe liver damage may occur if you take
more than 4,000 mg of acetaminophen in 24 hours

with other drugs containing acetaminophen

3 or more alcoholic drinks every day while using this product

directions

do not take more than directed (see overdose warning)
adults and children 12 years and over: take 2 caplets every 6 hours while symptoms last
swallow whole – do not crush, chew, or dissolve
do not take more than 6 caplets in 24 hours, unless directed by a doctor
do not use for more than 10 days unless directed by a doctor
children under 12 years : ask a doctor

INACTIVE INGREDIENT

LACTOSE MONOHYDRATE

INACTIVE INGREDIENT

STARCH, CORN

INACTIVE INGREDIENT

GELATIN

INACTIVE INGREDIENT

METHYLPARABEN

INACTIVE INGREDIENT

PROPYLPARABEN

INACTIVE INGREDIENT

MAGNESIUM STEARATE

INACTIVE INGREDIENT

TALC

INACTIVE INGREDIENT

SODIUM STARCH GLYCOLATE TYPE A POTATO

INACTIVE INGREDIENT

SILICON DIOXIDE

PACKAGE LABEL

Enter section text here